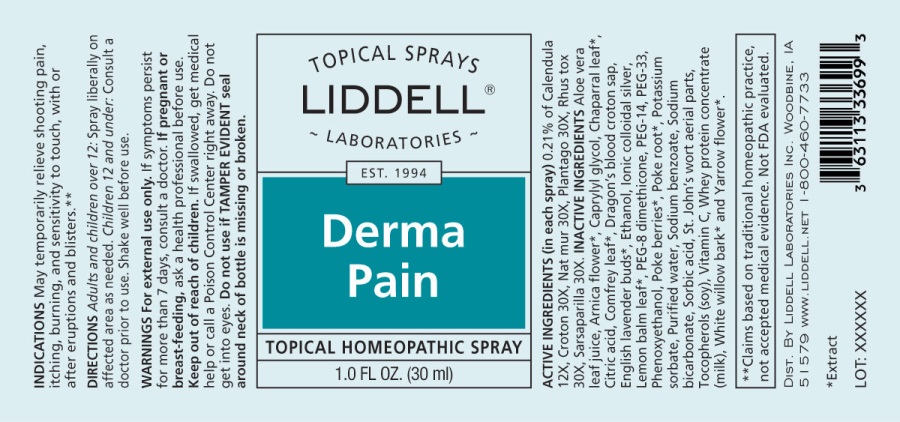 DRUG LABEL: Derma Pain
NDC: 50845-0280 | Form: SPRAY
Manufacturer: Liddell Laboratories, Inc.
Category: homeopathic | Type: HUMAN OTC DRUG LABEL
Date: 20241104

ACTIVE INGREDIENTS: CALENDULA OFFICINALIS FLOWERING TOP 12 [hp_X]/1 mL; CROTON TIGLIUM SEED 30 [hp_X]/1 mL; SODIUM CHLORIDE 30 [hp_X]/1 mL; PLANTAGO MAJOR WHOLE 30 [hp_X]/1 mL; TOXICODENDRON PUBESCENS LEAF 30 [hp_X]/1 mL; SMILAX ORNATA ROOT 30 [hp_X]/1 mL
INACTIVE INGREDIENTS: ALOE VERA LEAF; ARNICA MONTANA FLOWER; LARREA TRIDENTATA LEAF; CITRIC ACID MONOHYDRATE; COMFREY LEAF; CROTON LECHLERI RESIN; LAVANDULA ANGUSTIFOLIA SUBSP. ANGUSTIFOLIA FLOWER; ALCOHOL; SILVER; MELISSA OFFICINALIS LEAF; POLYETHYLENE GLYCOL 1600; PEG-8 DIMETHICONE; POLYETHYLENE GLYCOL 700; PHENOXYETHANOL; CAPRYLYL GLYCOL; SORBIC ACID; PHYTOLACCA AMERICANA FRUIT; PHYTOLACCA AMERICANA ROOT; POTASSIUM SORBATE; WATER; SODIUM BENZOATE; SODIUM BICARBONATE; HYPERICUM PERFORATUM; .ALPHA.-TOCOPHEROL; ASCORBIC ACID; WHEY; SALIX ALBA BARK; ACHILLEA MILLEFOLIUM FLOWER

DRUG FACTS:

ACTIVE INGREDIENTS:

(in each spray) 0.21% of Calendula Officinalis 12X, Croton Tiglium 30X, Natrum Muriaticum 30X, Plantago Major 30X, Rhus Tox 30X, Sarsaparilla (Smilax Regelii) 30X.

INDICATIONS:

May temporarily relieve shooting pain, itching, burning, and sensitivity to touch, with or after eruptions and blisters.**

**Clains based on traditional homeopathic practice, not accepted medical evidence. Not FDA evaluated.

WARNINGS:

For external use only.

If symptoms persist for more than 7 days, consult a doctor.

If pregnant or breast feeding, ask a health professional before use.

Keep out of reach of children. If swallowed, get medical help or call a Poison Control Center right away.

Do not get into eyes

Do not use if TAMPER EVIDENT seal around neck of bottle is missing or broken.

Keep out of reach of children. If swallowed, get medical help or call a Poison Control Center right away.

DIRECTIONS:

Adults and children over 12: Spray liberally on affected area as needed. Children 12 and under: Consult a doctor prior to use.

Shake well before use.

INDICATIONS:

May temporarily relieve shooting pain, itching, burning, and sensitivity to touch, with or after eruptions and blisters.**

**Clains based on traditional homeopathic practice, not accepted medical evidence. Not FDA evaluated.

INACTIVE INGREDIENTS:

Aloe Vera Leaf Juice, Arnica Flower*, Chaparral Leaf*, Citric Acid, Comfrey Leaf*, Dragon's Blood Croton (Sap), English Lavender (Buds)*, Ethanol, Ionic Colloidal Silver, Lemon Balm Leaf*, PEG-33, PEG-8 Dimethicone, PEG-14, Phenoxyethanol, Caprylyl Glycol, Sorbic Acid, Poke Berries*, Poke Root*, Potassium Sorbate, Purified Water, Sodium Bicarbonate, St. John's Wort Aerial Parts, Tocopherols (Vitamin E Oil), Vitamin C, Whey Protein Concentrate, White Willow Bark*, Yarrow Flower*.

QUESTIONS:

DIST. BY LIDDELL LABORATORIES INC. WOODBINE, IA

51579 WWW.LIDDELL.NET 1-800-460-7733

*Extract

PACKAGE LABEL DISPLAY:

TOPICAL SPRAYS

LIDDELL

LABORATORIES

EST 1994

Derma Pain

TOPICAL HOMEOPATHIC SPRAY

1.0 FL. OZ. (30 ml)